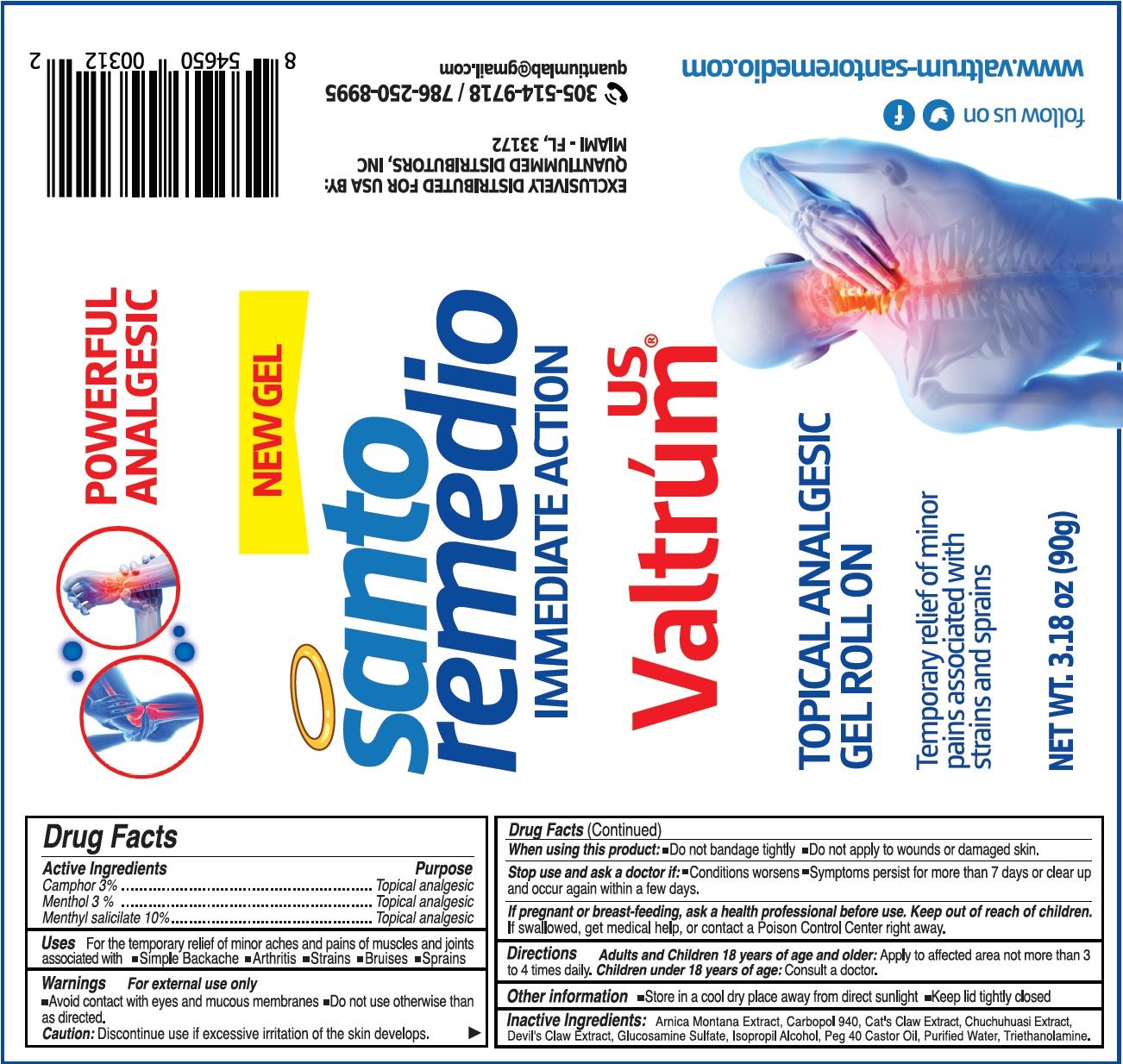 DRUG LABEL: Valtrum Analgesic
NDC: 75849-312 | Form: GEL
Manufacturer: Laboratorios Quantium LLC
Category: otc | Type: HUMAN OTC DRUG LABEL
Date: 20210819

ACTIVE INGREDIENTS: CAMPHOR (SYNTHETIC) 30 mg/1 g; MENTHOL 30 mg/1 g; MENTHYL SALICYLATE, (+/-)- 100 mg/1 g
INACTIVE INGREDIENTS: CAT'S CLAW; MAYTENUS KRUKOVII BARK; ARNICA MONTANA WHOLE; CARBOMER HOMOPOLYMER TYPE C (ALLYL PENTAERYTHRITOL CROSSLINKED); GLUCOSAMINE SULFATE; ISOPROPYL ALCOHOL; PEG-40 CASTOR OIL; WATER; TROLAMINE; HARPAGOPHYTUM PROCUMBENS ROOT

Valtrum Topical Analgesic Gel

Active Ingredients

Camphor 3%
Menthol 3%
Menthyl salicilate 10%

Purpose

Topical analgesic

Uses

For the temporary relief of minor aches and pains of muscles and joints associated with

• Simple Backache • Arthritis • Strains • Bruises • Sprains

Warnings

For external use only

- Avoid contact with eyes and mucous membranes
- Do not use otherwise than as directed.

Caution: Discontinue use if excessive irritation of the skin develops.

When using this product:

- Do not bandage tightly
- Do not apply to wounds or damaged skin.

Stop use and ask a doctor if:

- Conditions worsens
- Symptoms persist for more than 7 days or clear up and occur again within a few days.

If pregnant or breast-feeding,

ask a health professional before use.

Keep out of reach of children.

If swallowed, get medical help, or contact a Poison Control Center right away.

Directions

Adults and Children 18 years of age and older: Apply to affected area not more than 3 to 4 times daily. Children under 18 years of age: Consult a doctor.

Other information

- Store in a cool dry place away from direct sunlight
- Keep lid tightly closed

Inactive Ingredients:

Arnica Montana Extract, Carbopol 940, Cat's Claw Extract, Chuchuhuasi Extract, Devil's Claw Extract, Glucosamine Sulfate, Isopropil Alcohol, Peg 40 Castor Oil, Purified Water, Triethanolamine.